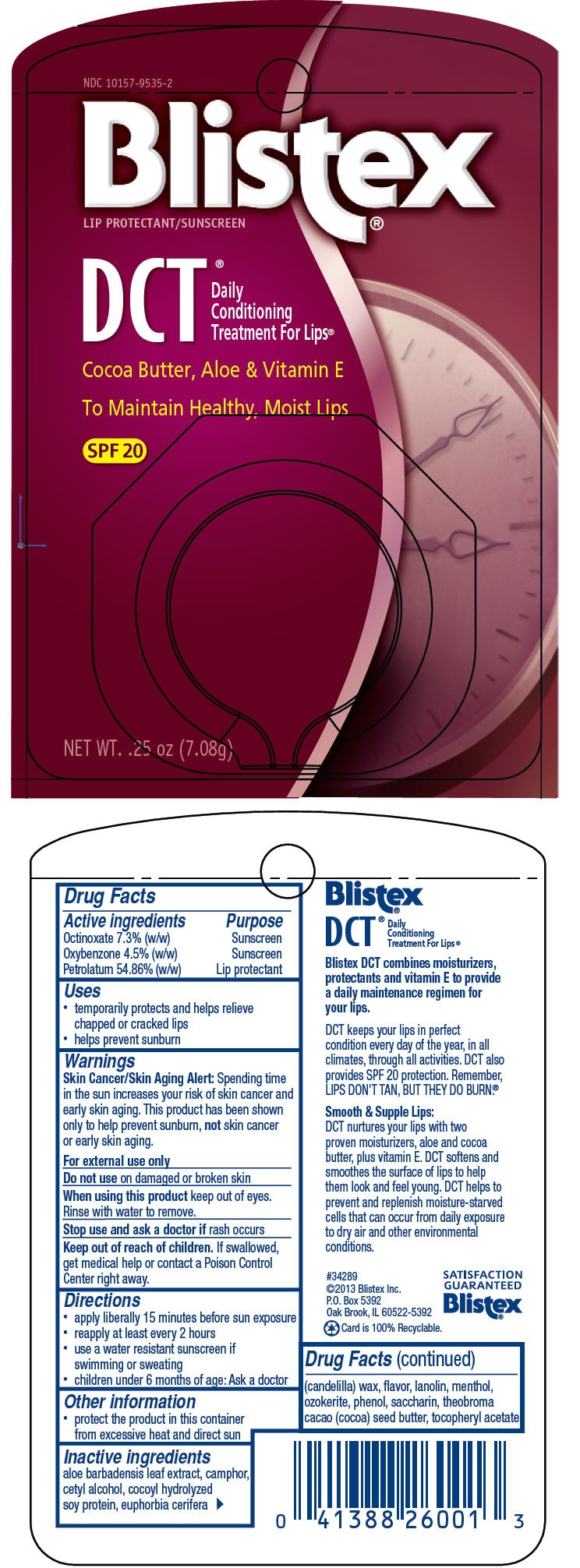 DRUG LABEL: Blistex 
NDC: 10157-9535 | Form: PASTE
Manufacturer: Blistex Inc.
Category: otc | Type: HUMAN OTC DRUG LABEL
Date: 20140106

ACTIVE INGREDIENTS: Petrolatum 54.86 g/100 g; Octinoxate 7.3 g/100 g; Oxybenzone 4.5 g/100 g
INACTIVE INGREDIENTS: LANOLIN; CERESIN; CANDELILLA WAX; Cocoa Butter; CETYL ALCOHOL; ALOE VERA LEAF; Menthol; Phenol; CAMPHOR (SYNTHETIC); .ALPHA.-TOCOPHEROL ACETATE; SACCHARIN

Blistex®
Daily Conditioning Treatment

Drug Facts

ACTIVE INGREDIENT

Active ingredients | Purpose
Octinoxate 7.3% (w/w) | Sunscreen
Oxybenzone 4.5% (w/w) | Sunscreen
Petrolatum 54.86% (w/w) | Lip protectant

Uses

- temporarily protects and helps relieve chapped or cracked lips
- helps prevent sunburn

Warnings

Skin Cancer/Skin Aging Alert

Spending time in the sun increases your risk of skin cancer and early skin aging. This product has been shown only to help prevent sunburn, not skin cancer or early skin aging.

For external use only

Do not use on damaged or broken skin

When using this product keep out of eyes. Rinse with water to remove.

Stop use and ask a doctor if rash occurs

Keep out of reach of children. If swallowed, get medical help or contact a Poison Control Center right away.

Directions

- apply liberally 15 minutes before sun exposure
- reapply at least every 2 hours
- use a water resistant sunscreen if swimming or sweating
- children under 6 months of age: Ask a doctor

Other information

- protect the product in this container from excessive heat and direct sun

Inactive ingredients

aloe barbadensis leaf extract, camphor, cetyl alcohol, cocoyl hydrolyzed soy protein, euphorbia cerifera (candelilla) wax, flavor, lanolin, menthol, ozokerite, phenol, saccharin, theobroma cacao (cocoa) seed butter, tocopheryl acetate

PRINCIPAL DISPLAY PANEL - 7.08 g Jar Blister Pack

NDC 10157-9535-2

Blistex®
LIP PROTECTANT/SUNSCREEN

DCT ®

Daily
Conditioning
Treatment For Lips®

Cocoa Butter, Aloe & Vitamin E

To Maintain Healthy, Moist Lips

SPF 20

NET WT. .25 oz (7.08g)